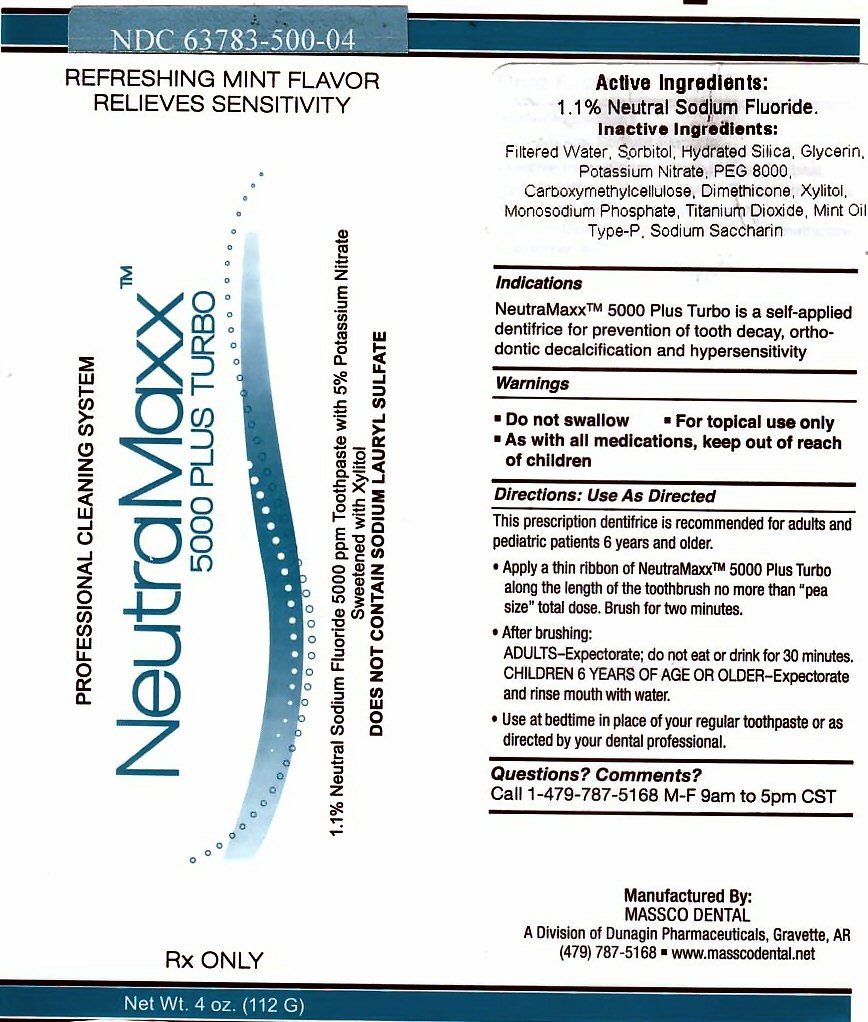 DRUG LABEL: NEUTRAMAXX 5000 PLUS TURBO
NDC: 63783-500 | Form: PASTE
Manufacturer: Massco Dental A Division of Dunagin Pharmaceuticals
Category: prescription | Type: HUMAN PRESCRIPTION DRUG LABEL
Date: 20231217

ACTIVE INGREDIENTS: SODIUM FLUORIDE 1.1 g/112 g
INACTIVE INGREDIENTS: WATER; SORBITOL; HYDRATED SILICA; GLYCERIN; XYLITOL; POTASSIUM NITRATE; MINT; POLYETHYLENE GLYCOL 8000; CARBOXYMETHYLCELLULOSE; TITANIUM DIOXIDE; SACCHARIN SODIUM; DIMETHICONE; POLOXAMER 407

ACTIVE INGREDIENT SECTION

DRUG FACTS ACTIVE INGREDIENT 1.1 % NEUTRAL SODIUM FLUORIDE

INACTIVE INGREDIENT SECTION

INACTIVE INGREDIENTS: FILTERED WATER, SORBITAL, HYDRATED SILICA, GLYCERINE, XYLITOL, POTASSIUM NITRATE, MINT FLAVOR, PEG,CARBOXYMETHYLCELLULOSE, TITANIUM DIOXIDE, SODIUM SACCHARIN, DIMETHICONE, POLOXOMER 407

INDICATIONS SECTION

INDICATIONS NEUTRAMAXXtm 5000 PLUS TURBO IS A SELF-APPLIED DENTIFRICE FOR PREVENTION OF TOOTH DECAY, ORTHODONTIC DECALCIFICATION AND HYPERSENSITIVITY

WARNINGS SECTION

DO NOT SWALLOW FOR TOPICAL USE ONLY AS WITH ALL MEDICATIONS, KEEP OUT OF REACH OF CHILDREN

KEEP OUT OF REACH OF CHILDREN SECTION

AS WITH ALL MEDICATIONS, KEEP OUT OF REACH OF CHILDREM

DIRECTIONS: USE AS DIRECTED

THIS PRESCRIPTION DENTIFRICE IS RECOMMENDED FOR ADULTS AND PEDIATRIC PATIENTS 6 YEARS AND OLDER.

APPLY A THIN RIBBON OF NEUTRAMAXXtm 500 PLUS TURBO ALONG THE LENGTH OF THE TOOTHBRUSH NO MORE THAN "PEA SIZE" TOTAL DOSE. BRUSH FOR 2 MINUTES

AFTER BRUSHING ADULTS-EXPECTORATE; DO NOT EAT OR DRINK FOR 30 MINUTES

CHILDREN 6 YEARS OF AGE OR OLDER-EXPECTORATE AND RINSE MOUTH WITH WATER

USE AT BEDTIME IN PLACE OF YOUR REGULAR TOOTHPASTE OR AS DIRECTED BY YOUR DENTAL PROFESSIONAL.

QUESTIONS? COMMENTS? SECTION

CALL 1-479-5168 M-F 9AM TO 5PM CST

PACKAGE LABEL

PROFESSIONAL CLEANING SYSTEM NEUTRAMAXXtm 5000 PLUS TURBO REFRESHING MINT FLAVOR RELIEVES SENSITIVITY

1.1% NEUTRAL SODIUM FLUORIDE 5000PPM TOOTHPASTE WITH 5% POTASSIUM NITRATE SWEETENED WITH XYLITOL DOES NOT CONTAIN SODIUM LAURYL SULFATE RX ONLY NET WT. 4 OZ (112 G) NDC 63783-3233-112

MAUNFACTURES BY: MASSCO DENTAL A DIVISION OF DUNAGIN PHARMACEUTICALS, GRAVETTE, ar (479) 787-5168 WWW.MASSCODENTAL.NET

res